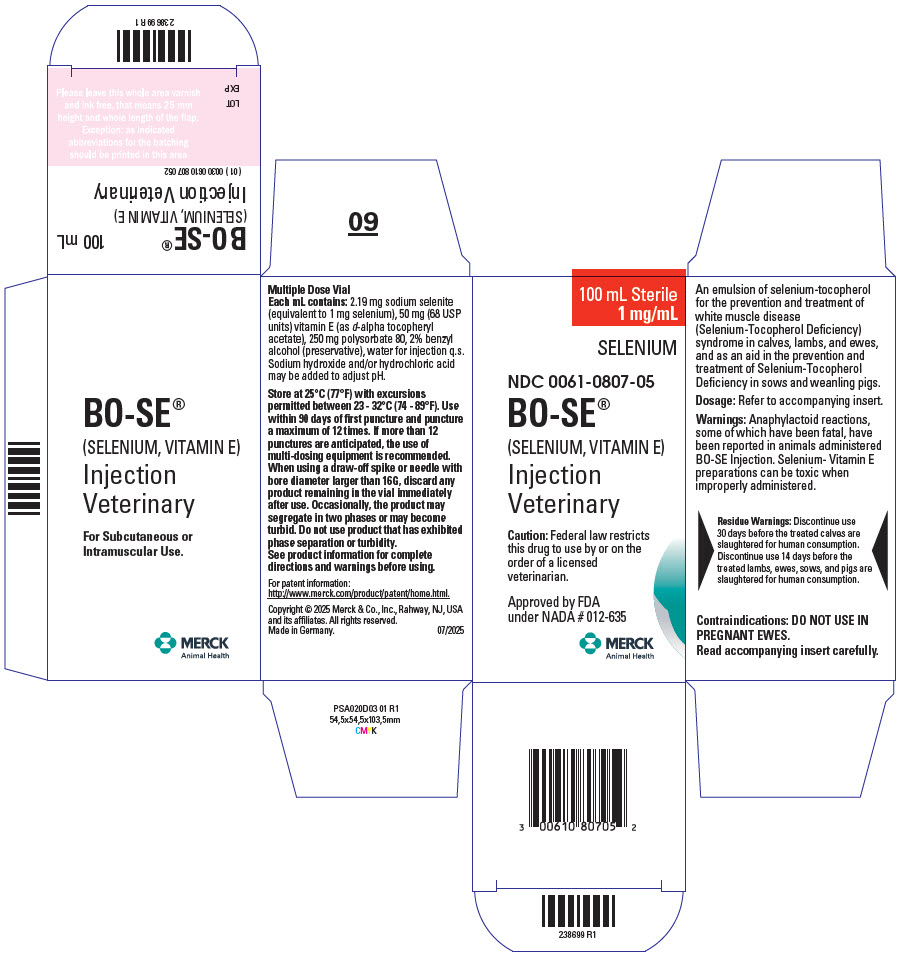 DRUG LABEL: BO-SE
NDC: 0061-0807 | Form: INJECTION, SOLUTION
Manufacturer: Merck Sharp & Dohme Corp.
Category: animal | Type: PRESCRIPTION ANIMAL DRUG LABEL
Date: 20251124

ACTIVE INGREDIENTS: SODIUM SELENITE 1 mg/1 mL; .ALPHA.-TOCOPHEROL ACETATE, D- 68 [USP'U]/1 mL

BO-SE®
(SELENIUM, VITAMIN E)
Injection

FOR VETERINARY USE ONLY

PRODUCT
INFORMATION

CAUTION Federal law restricts this drug to use by or on the order of a licensed veterinarian.

DESCRIPTION

DESCRIPTION BO-SE (selenium, vitamin E) is an emulsion of selenium-tocopherol for the prevention and treatment of white muscle disease (Selenium-Tocopherol Deficiency) syndrome in calves, lambs, and ewes, and as an aid in the prevention and treatment of Selenium-Tocopherol Deficiency in sows and weanling pigs. Each mL contains: 2.19 mg sodium selenite (equivalent to 1 mg selenium), 50 mg (68 USP units) vitamin E (as d-alpha tocopheryl acetate), 250 mg polysorbate 80, 2% benzyl alcohol (preservative), water for injection q.s. Sodium hydroxide and/or hydrochloric acid may be added to adjust pH.

CLINICAL PHARMACOLOGY

PHARMACOLOGY It has been demonstrated that selenium and tocopherol exert physiological effects and that these effects are intertwined with sulfur metabolism. Additionally, tocopherol appears to have a significant role in the oxidation process, thus suggesting an interrelationship between selenium and tocopherol in overcoming sulfur induced depletion and restoring normal metabolism. Although oral ingestion of adequate amounts of selenium and tocopherol would seemingly restore normal metabolism, it is apparent that the presence of sulfur and, perhaps, other factors interfere during the digestive processwith proper utilization of selenium and tocopherol. When selenium and tocopherol are injected, they bypass the digestive process and exert their full metabolic effects promptly on cell metabolism. Anti-inflammatory action has been demonstrated by selenium-tocopherol in the Selye Pouch Technique and experimentally induced polyarthritis study in rats.

VETERINARY INDICATIONS

INDICATIONS BO-SE (selenium, vitamin E) is recommended for the prevention and treatment of white muscle disease (Selenium-Tocopherol Deficiency) syndrome in calves, lambs, and ewes. Clinical signs are: stiffness and lameness, diarrhea and unthriftiness, pulmonary distress and/or cardiac arrest. In sows and weanling pigs, as an aid in the prevention and treatment of diseases associated with Selenium-Toco pherol deficiency, such as hepatic necrosis, mulberry heart disease, and white muscle disease. Where known deficiencies of selenium and/or vitamin E exist, it is advisable, from the prevention and control standpoint, to inject the sow during the last week of pregnancy.

CONTRAINDICATIONS

CONTRAINDICATIONS DO NOT USE IN PREGNANT EWES. Deaths and abortions have been reported in pregnant ewes injected with this product.

WARNINGS

WARNINGS Anaphylactoid reactions, some of which have been fatal, have been reported in animals administered BO-SE Injection. Signs include excitement, sweating, trembling, ataxia, respiratory distress, and cardiac dysfunction. Selenium- Vitamin E preparations can be toxic when improperly administered.

RESIDUE WARNING

Residue Warnings: Discontinue use 30 days before the treated calves are slaughtered for human consumption. Discontinue use 14 days before the treated lambs, ewes, sows, and pigs are slaughtered for human consumption.

PRECAUTIONS

PRECAUTIONS Selenium-Tocopherol Deficiency (STD) syndrome produces a variety and complexity of symptoms often interfering with a proper diagnosis. Even in selenium deficient areas there are other disease conditions which produce similar clinical signs. It is imperative that all these conditions be carefully considered prior to treatment of STD syndrome. Serum selenium levels, elevated SGOT, and creatine levels may serve as aids in arriving at a diagnosis of STD, when associated with other indices. Selenium is toxic if administered in excess. A fixed dose schedule is therefore important (read package insert for each selenium-tocopherol product carefully before using).

ADVERSE REACTIONS

ADVERSE REACTIONS Reactions, including acute respiratory distress, frothing from the nose and mouth, bloating, severe depression, abortions, and deaths have occurred in pregnant ewes. Do not use product with phase separation or turbidity.

DOSAGE AND ADMINISTRATION Inject subcutaneously or intramuscularly. Calves: 2.5-3.75 mL per 100 pounds of body weight depending on the severity of the condition and the geographical area. Lambs 2 weeks of age and older: 1 mL per 40 pounds of body weight (minimum, 1 mL). Ewes: 2.5 mL per 100 pounds of body weight. Sows: 1 mL per 40 pounds of body weight. Weanling pigs: 1 mL per 40 pounds of body weight (minimum, 1 mL). Not for use in newborn pigs.

STORAGE AND HANDLING

Store at 25°C (77°F) with excursions permitted between 23 - 32°C (74 - 89°F).

Use within 90 days of first puncture and puncture a maximum of 12 times. If more than 12 punctures are anticipated, the use of multi-dosing equipment is recommended. When using a draw-off spike or needle with bore diameter larger than 16G, discard any product remaining in the vial immediately after use.

Occasionally, the product may segregate in two phases or may become turbid. Do not use product that has exhibited phase separation or turbidity.

HOW SUPPLIED

HOW SUPPLIED 100 mL sterile, multiple dose vial, NDC 0061-0807-05.

Approved by FDA under NADA # 012-635

Copyright ©2025 Merck & Co., Inc., Rahway, NJ, USA,and its affiliates.
All rights reserved.
Made in Germany.
Rev. 07/2025

MERCK
Animal Health

238700 R2

PRINCIPAL DISPLAY PANEL - 100 mL Vial Carton

100 mL Sterile
1 mg/mL

SELENIUM

NDC 0061-0807-05

BO-SE®
(SELENIUM, VITAMIN E)

Injection
Veterinary

Caution: Federal law restricts
this drug to use by or on the
order of a licensed
veterinarian.

Approved by FDA
under NADA # 012-635

MERCK
Animal Health